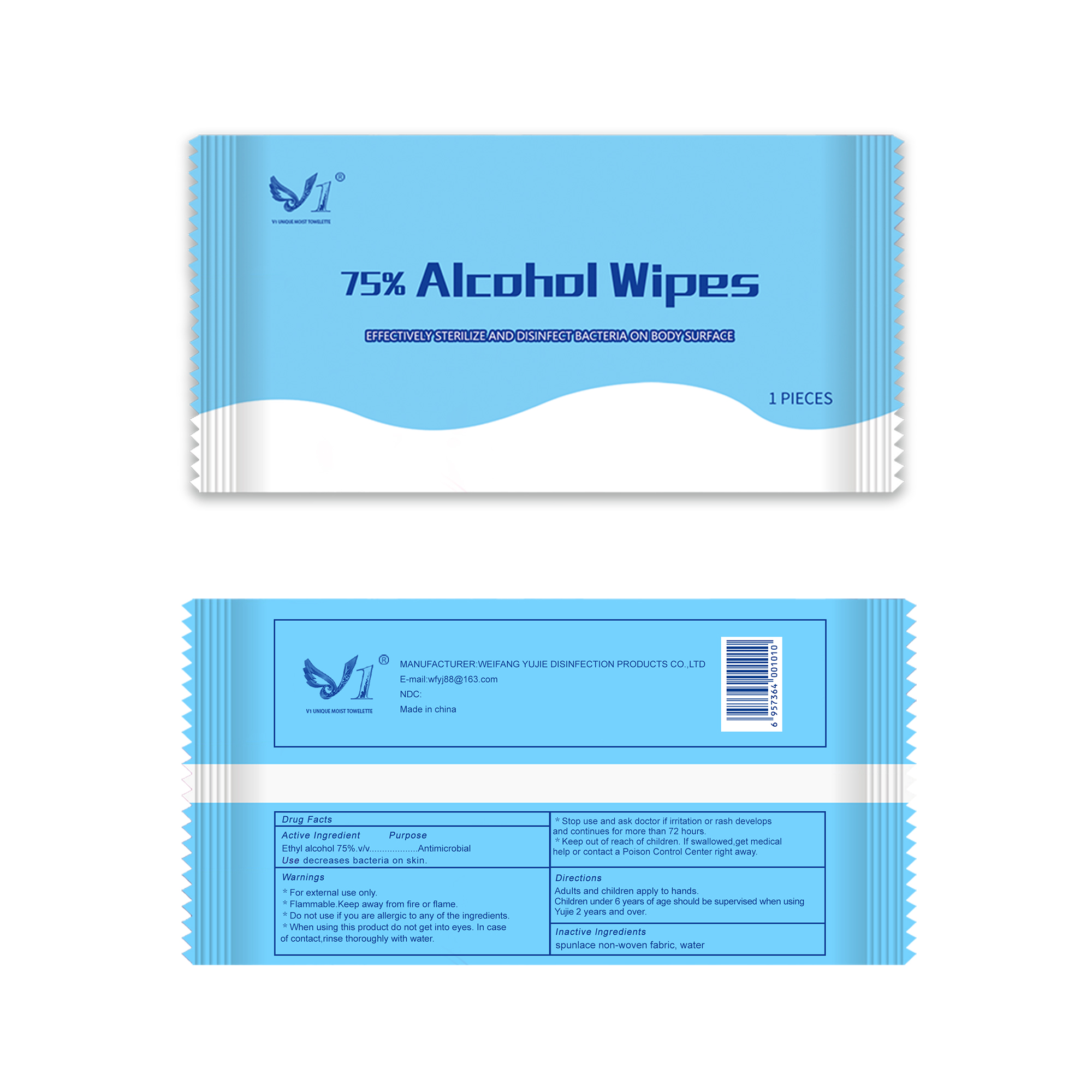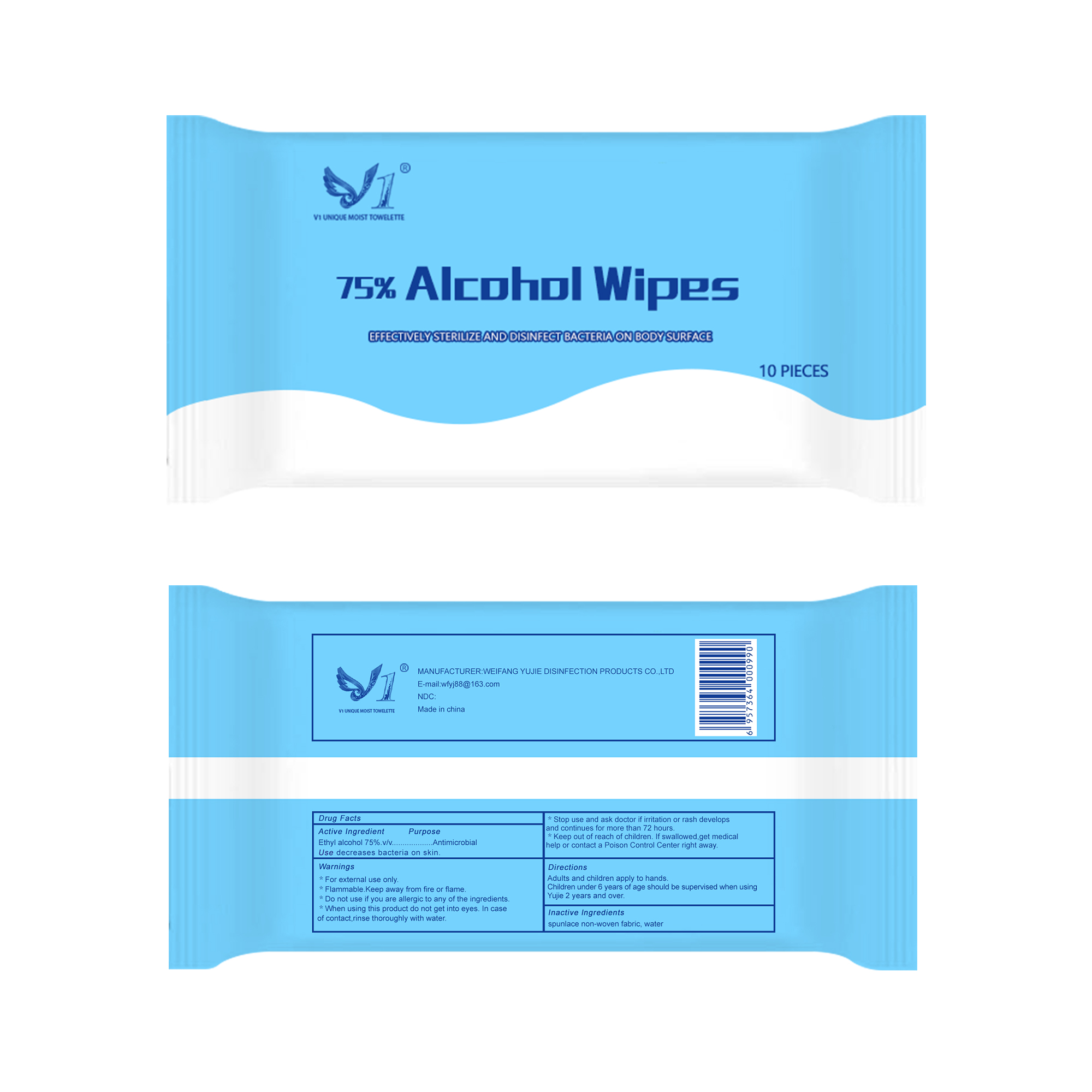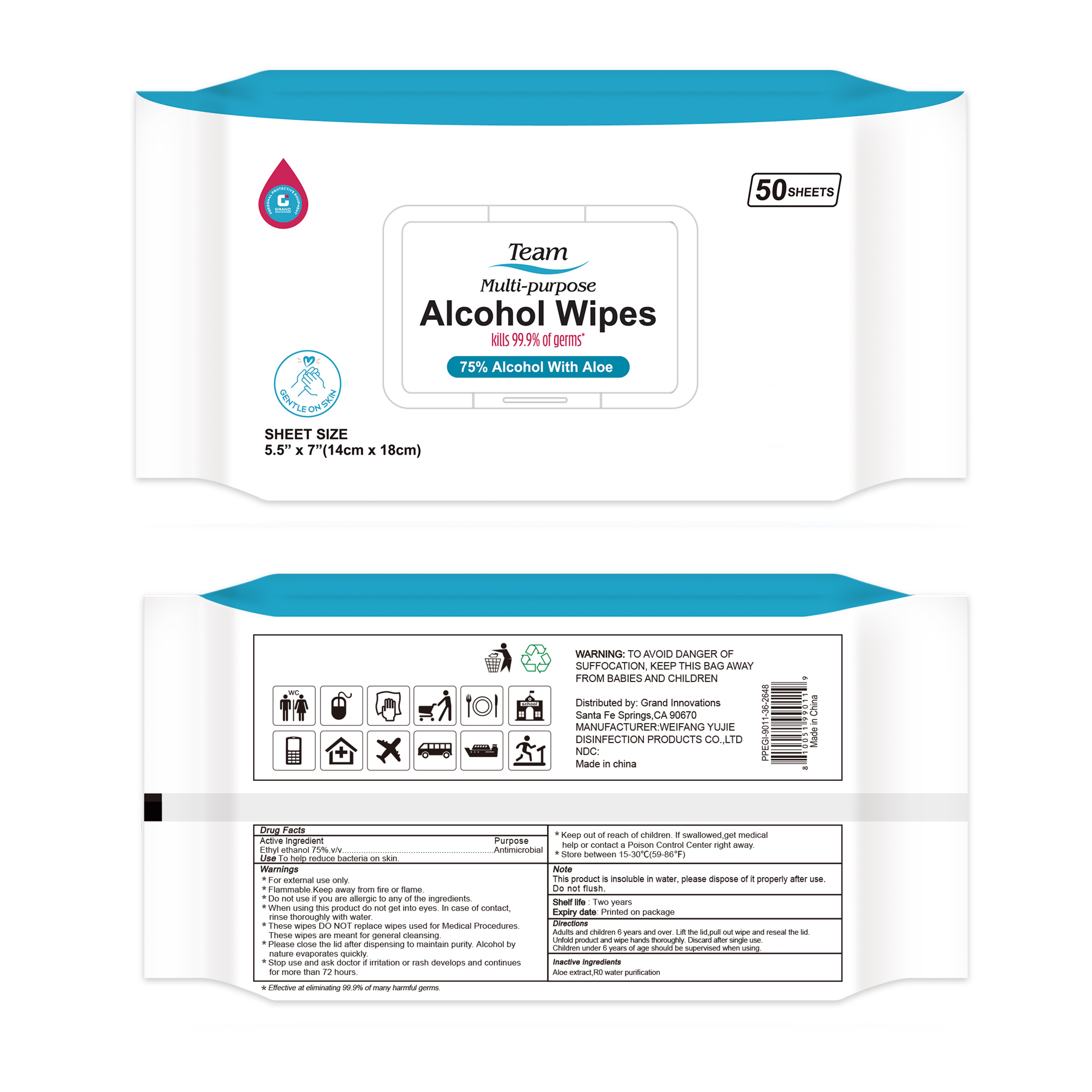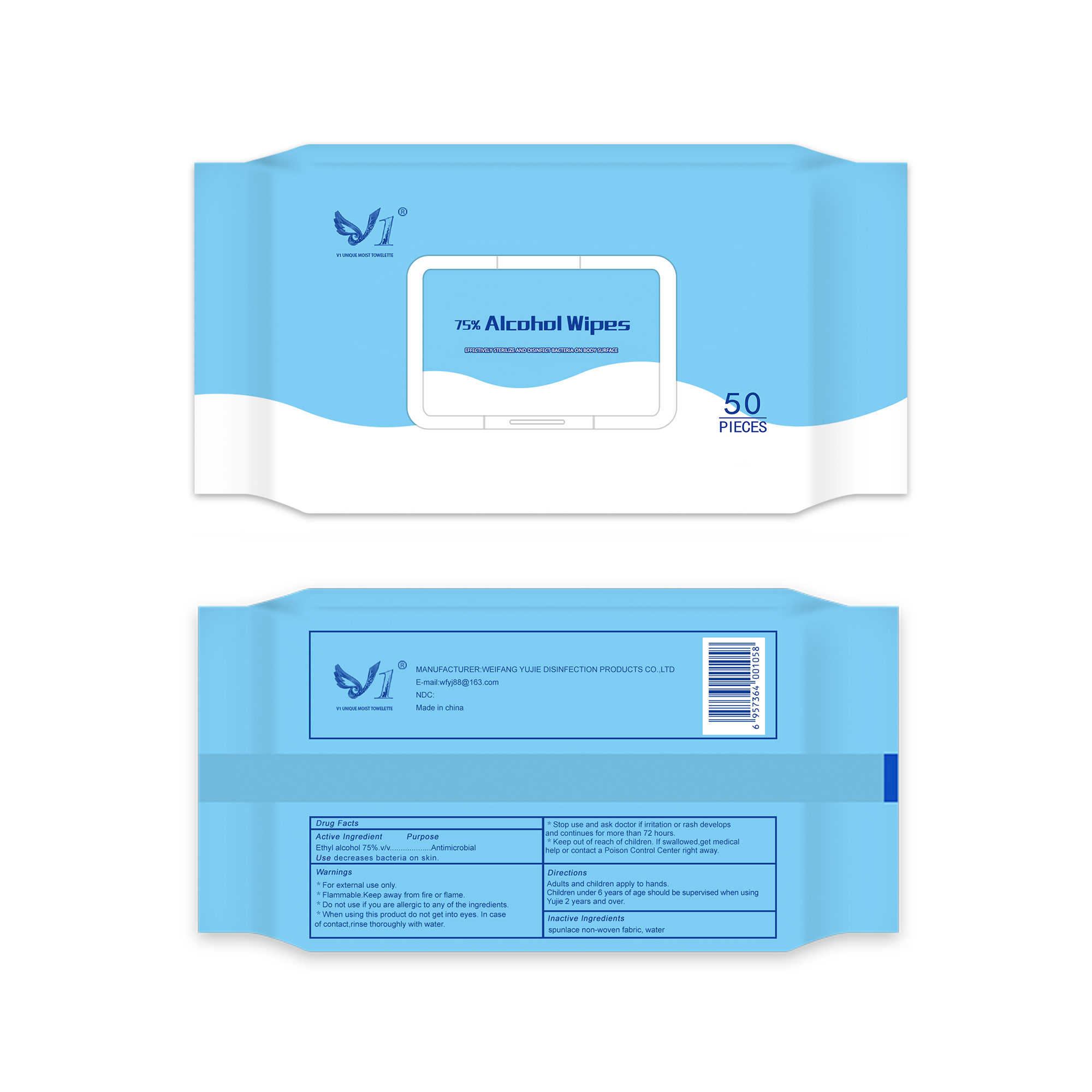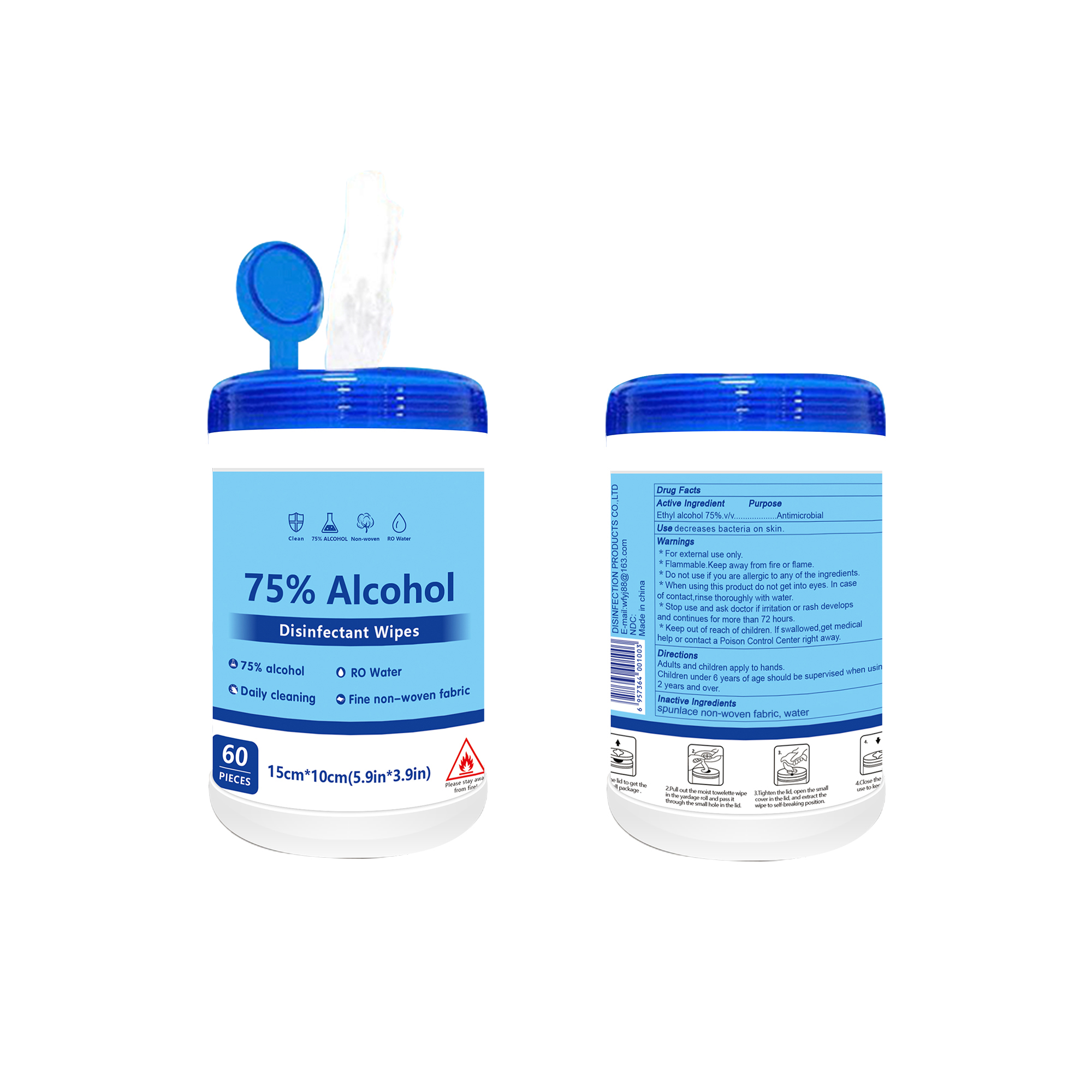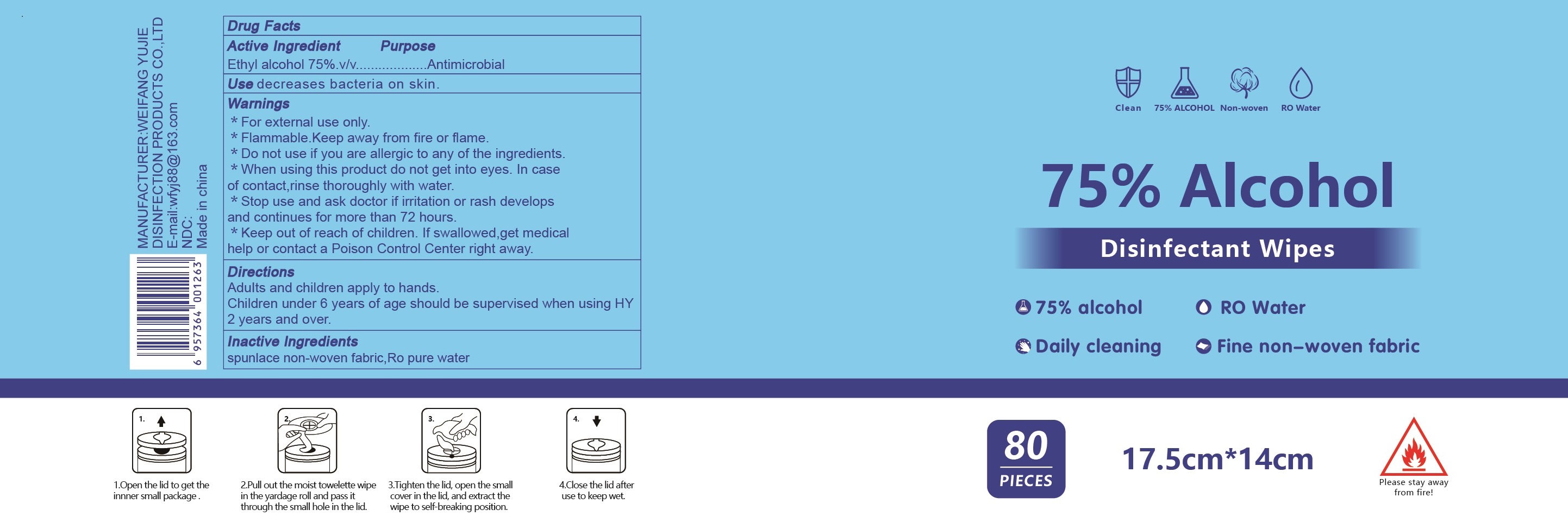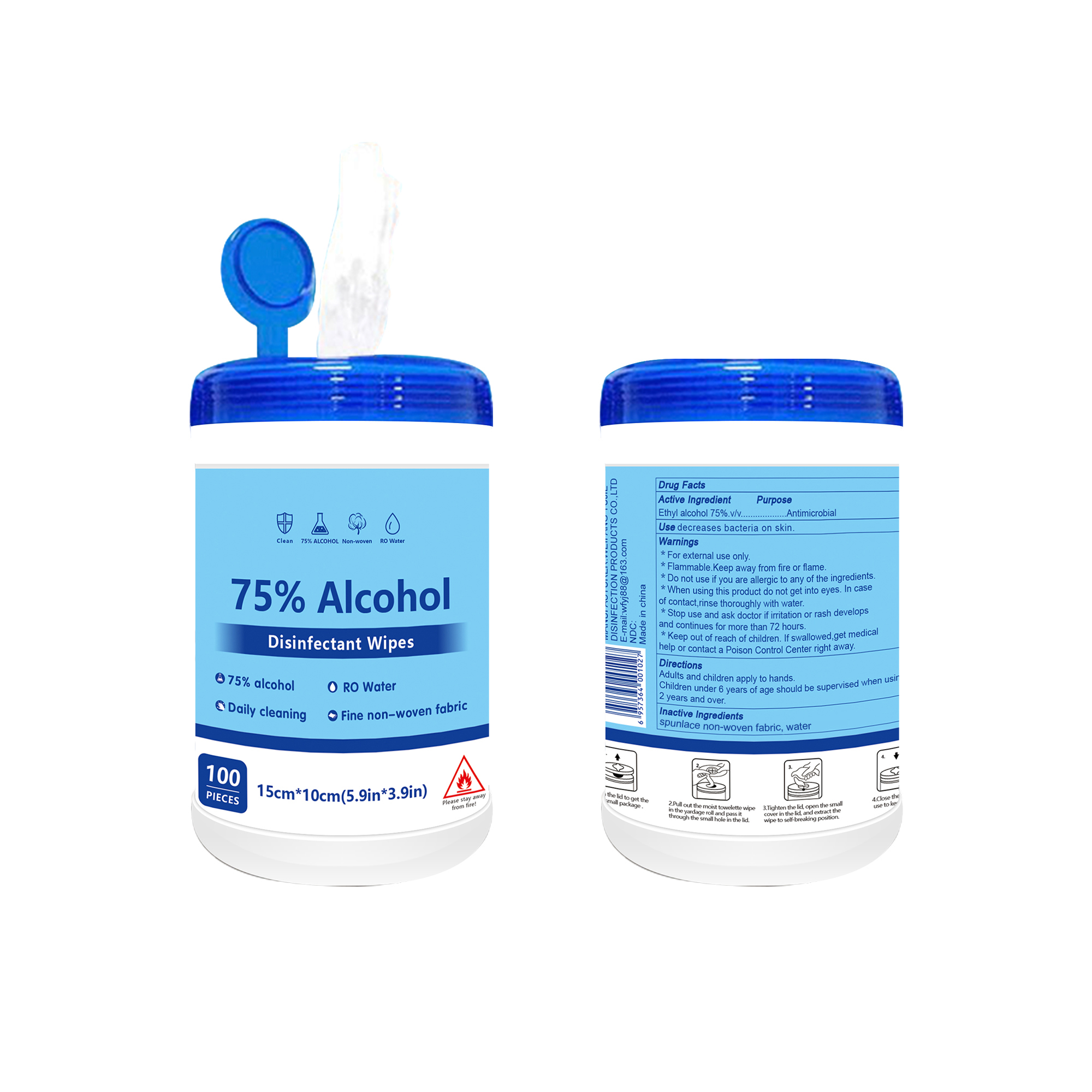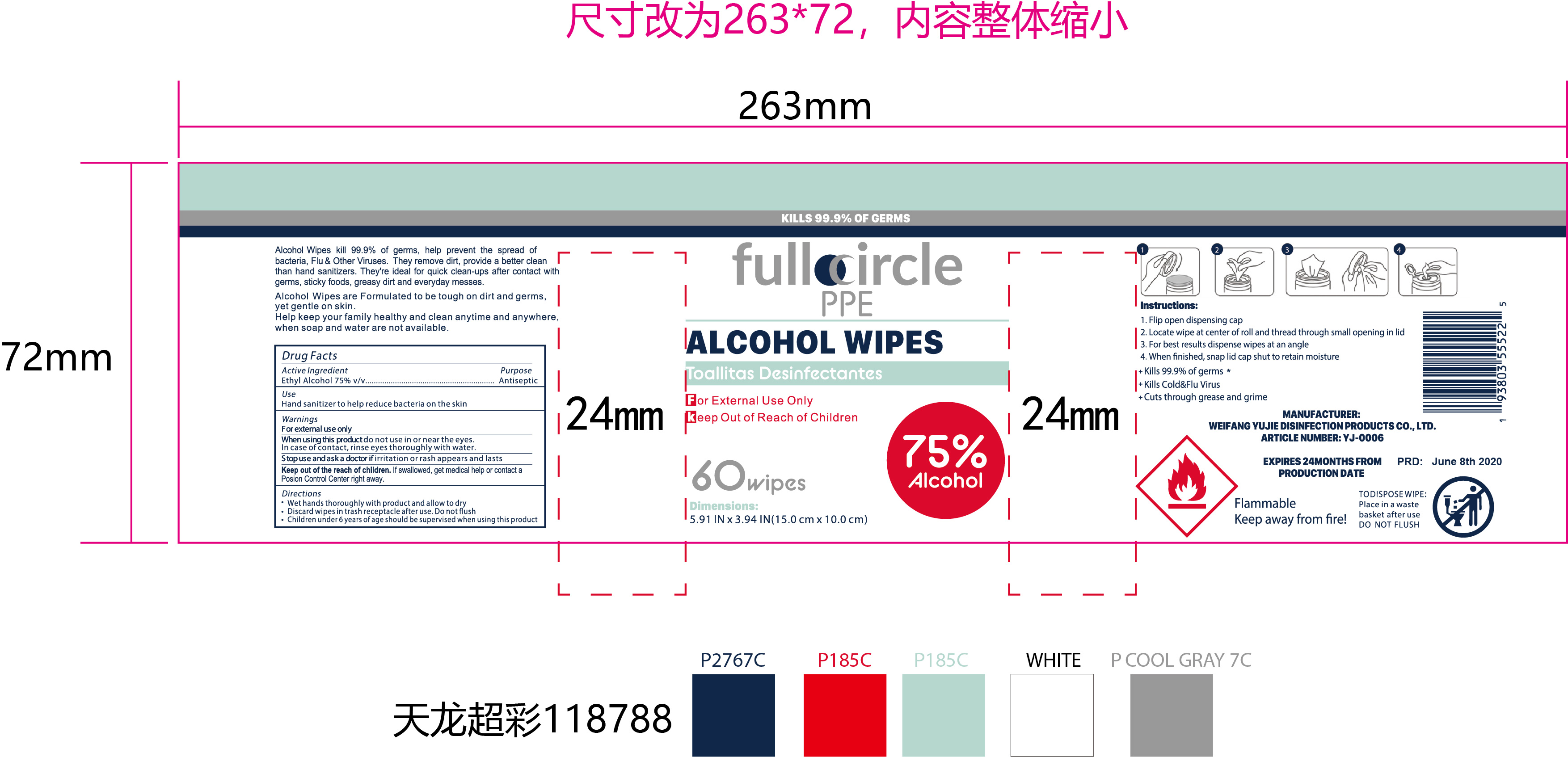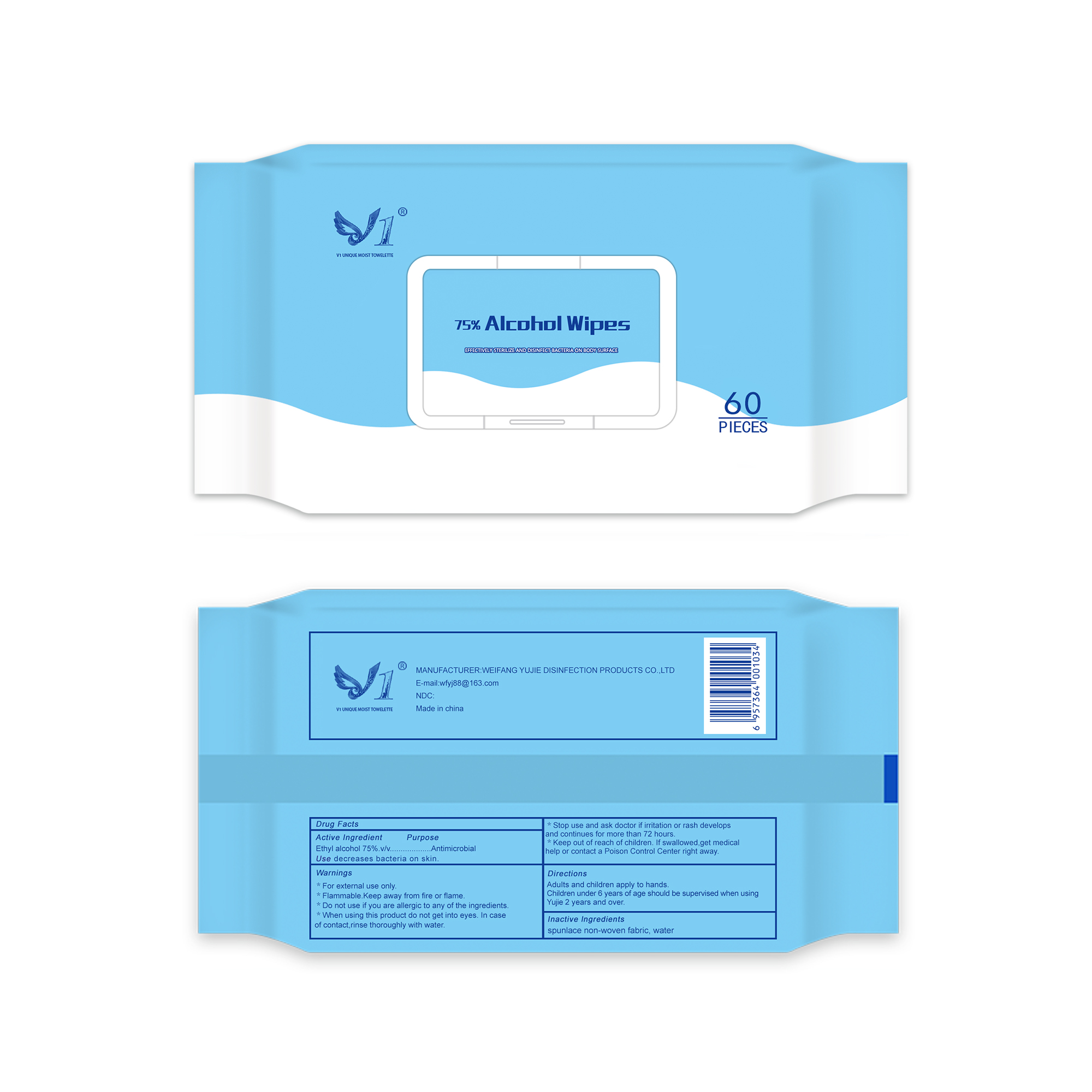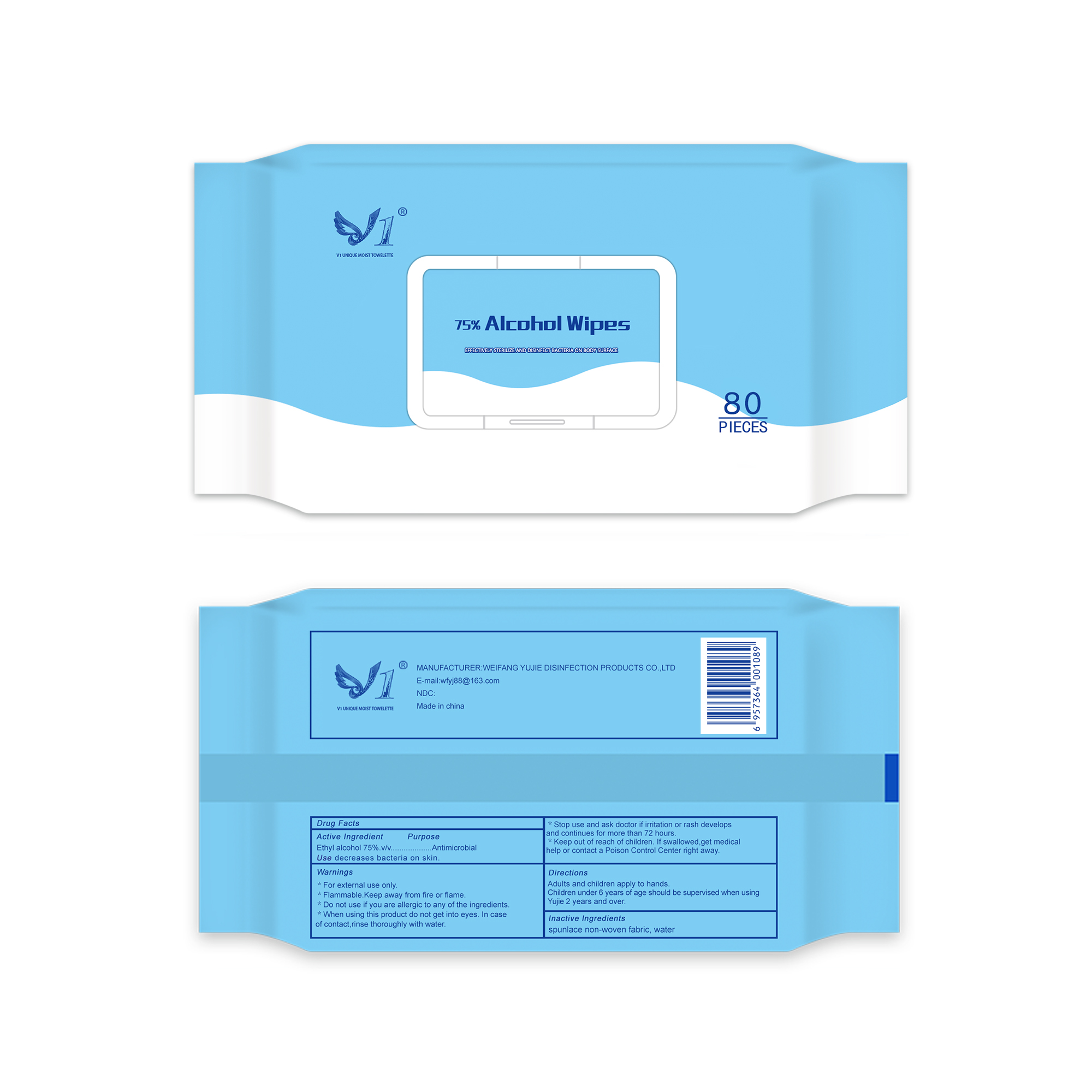 DRUG LABEL: ALCOHOL WIPES
NDC: 78959-001 | Form: CLOTH
Manufacturer: Weifang Yujie Disinfectant Co. , Ltd.
Category: otc | Type: HUMAN OTC DRUG LABEL
Date: 20201211

ACTIVE INGREDIENTS: ALCOHOL 75 mL/100 1
INACTIVE INGREDIENTS: WATER

78959-001
ALCOHOL WIPES

Active Ingredient

Ethyl alcohol 75%.v/v

Purpose

Antimicrobial

Use

decreases bacteria on skin.

Warnings

For external use only.

Flammable.Keep away from fire or flame.

Do not use

if you are allergic to any of the ingredients.

When using this product

do not get into eyes.In case of contact,rinse thoroughly with water.

Stop use and ask doctor

if irritation or rash develops and continues for more than 72 hours.

Keep out of reach of children

If swallowed,get medical help or contact a Poison Control Center right away.

Directions

Adults and children apply to hands.

Children under 6 years of age should be supervised when using HY 2 years and over.

Inactive Ingredients

Ro pure water, Double-chain quaternary ammonium salt.